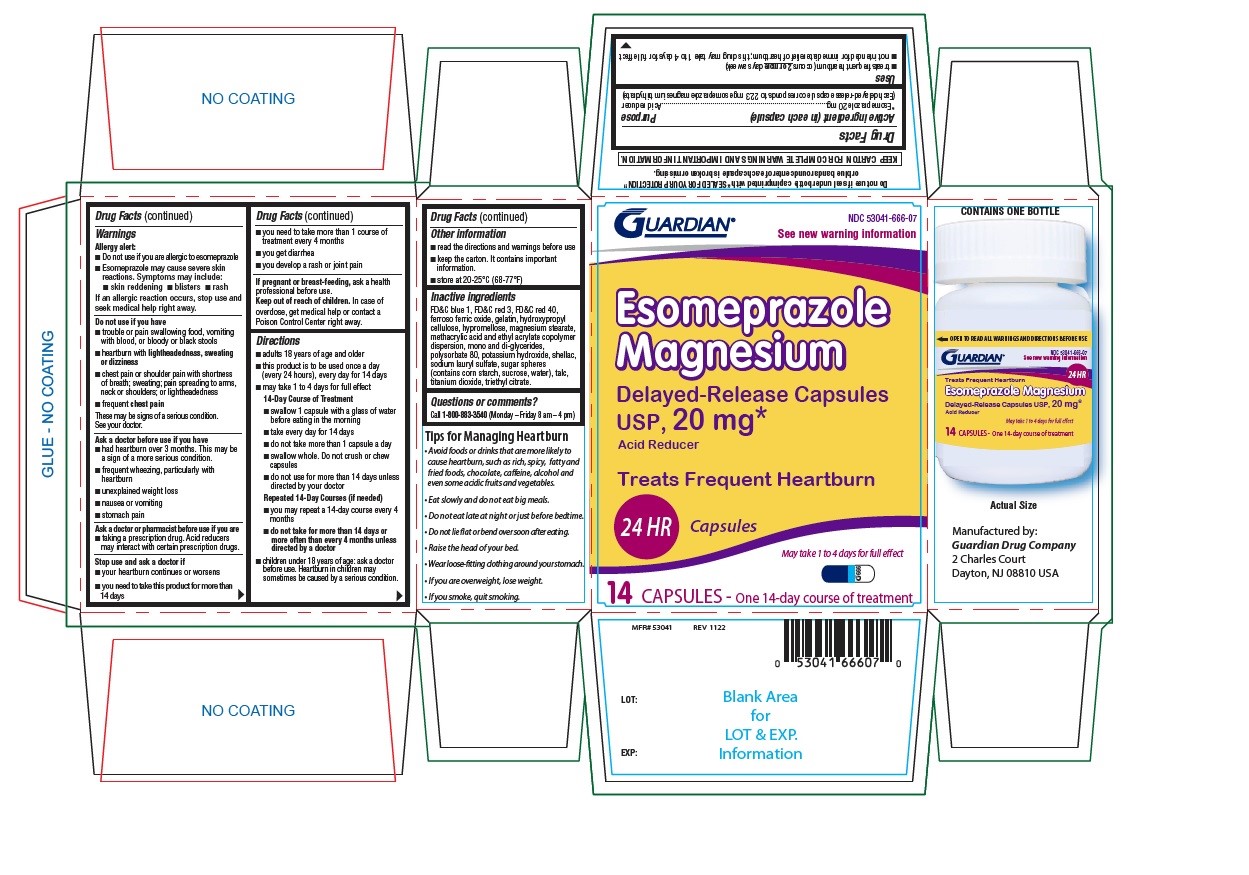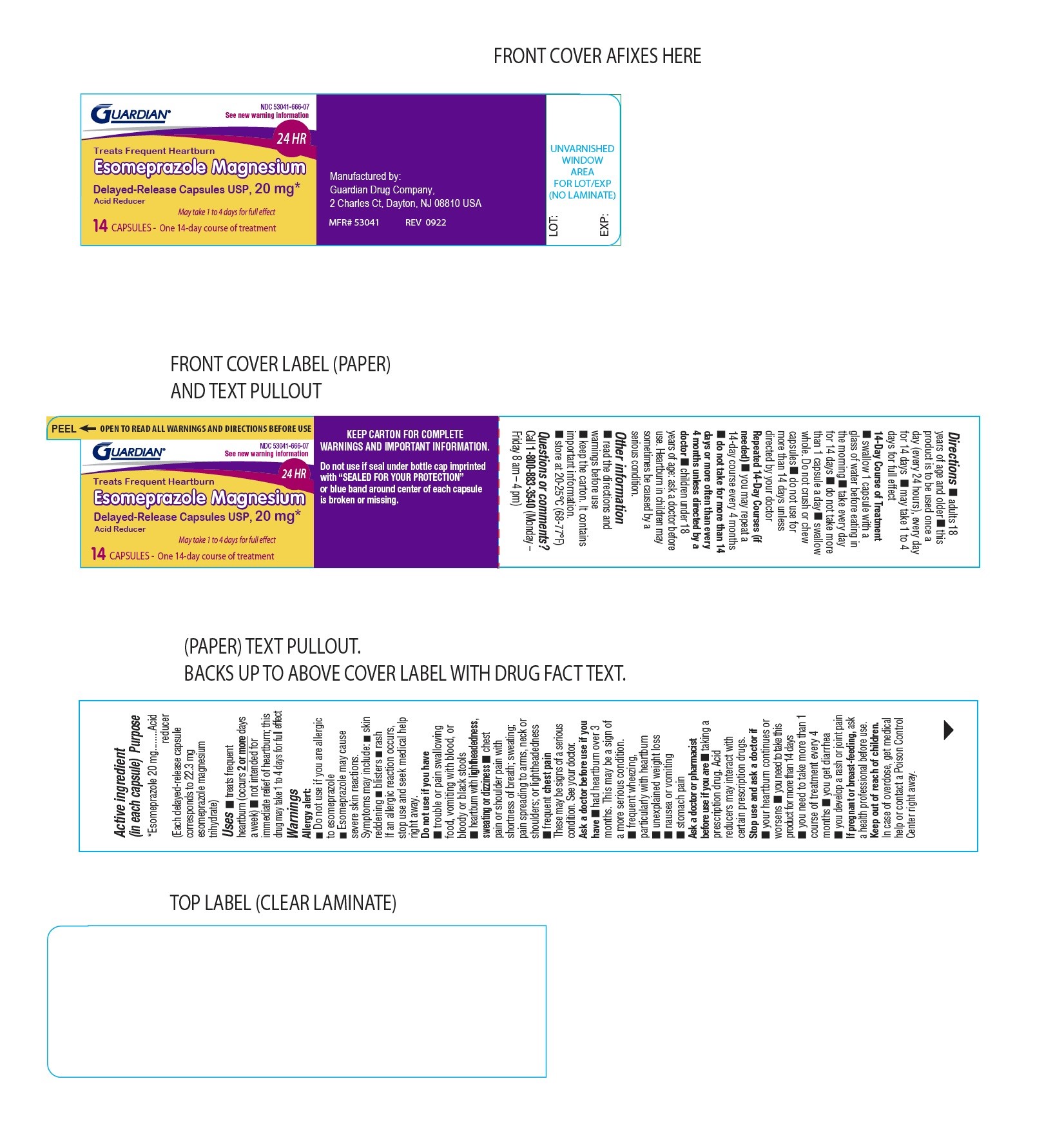 DRUG LABEL: Esomeprazole Magnesium
NDC: 53041-666 | Form: CAPSULE, DELAYED RELEASE
Manufacturer: Guardian Drug Company
Category: otc | Type: Human OTC Drug Label
Date: 20241218

ACTIVE INGREDIENTS: ESOMEPRAZOLE MAGNESIUM 20 mg/1 1
INACTIVE INGREDIENTS: FD&C BLUE NO. 1; FD&C RED NO. 3; FD&C RED NO. 40; FERROSOFERRIC OXIDE; GELATIN; HYDROXYPROPYL CELLULOSE; HYPROMELLOSE 2910 (6 MPA.S); MAGNESIUM STEARATE; METHACRYLIC ACID AND ETHYL ACRYLATE COPOLYMER; GLYCERYL MONO- AND DICAPRYLOCAPRATE; POLYSORBATE 80; POTASSIUM HYDROXIDE; SHELLAC; SODIUM LAURYL SULFATE; STARCH, CORN; SUCROSE; TALC; TITANIUM DIOXIDE; TRIETHYL CITRATE

Esomeprazole Magnesium Delayed Release Capsules

ACTIVE INGREDIENT(in each capsule)

*Esomeprazole 20 mg

(Each delayed-release capsule corresponds to 22.3 mg esomeprazole magnesium trihydrate)

PURPOSE

Acid reducer

USE(S)

- treats frequent heartburn (occurs 2 or more days a week)
- not intended for immediate relief of heartburn; this drug may take 1 to 4 days for full effect

WARNINGS

Allergy alert:

· Do not use if you are allergic to esomeprazole.

· Esomeprazole may cause severe skin reactions. Symptoms may include:

· skin reddening

· blisters

· rash

If an allergic reaction occurs, stop use and seek medical help right away.

DO NOT USE IF YOU HAVE

- trouble or pain swallowing food, vomiting with blood, or bloody or black stools
- heartburn with lightheadedness, sweating or dizziness
- chest pain or shoulder pain with shortness of breath; sweating; pain spreading to arms, neck or shoulders; or lightheadedness
- frequent chest pain

These may be signs of a serious condition. See your doctor.

ASK A DOCTOR BEFORE USE IF YOU HAVE

- had heartburn over 3 months. This may be a sign of a more serious condition.
- frequent wheezing, particularly with heartburn
- unexplained weight loss
- nausea or vomiting
- stomach pain

ASK A DOCTOR OR PHARMACIST BEFORE USE IF YOU ARE

- taking a prescription drug. Acid reducers may interact with certain prescription drugs.

STOP USE AND ASK DOCTOR IF

- your heartburn continues or worsens
- you need to take this product for more than 14 days
- you need to take more than 1 course of treatment every 4 months
- you get diarrhea
- you develop a rash or joint pain

IF PREGNANT OR BREAST-FEEDING

ask a health professional before use.

KEEP OUT OF REACH OF CHILDREN

In case of overdose, get medical help or contact a Poison Control Center right away.

DIRECTIONS

- adults 18 years of age and older
- this product is to be used once a day (every 24 hours), every day for 14 days
- may take 1 to 4 days for full effect

14-Day Course of Treatment

- swallow 1 capsule with a glass of water before eating in the morning

- take every day for 14 days
- do not take more than 1 capsule a day
- swallow whole. Do not crush or chew capsules
- do not use for more than 14 days unless directed by your doctor

Repeated 14-Day Courses (if needed)

- you may repeat a 14-day course every 4 months
- do not take for more than 14 days or more often than every 4 months unless directed by a doctor

- children under 18 years of age: ask a doctor before use. Heartburn in children may sometimes be caused by a serious condition.

OTHER INFORMATION

- read the directions and warnings before use
- keep the carton. It contains important information.
- store at 20-25ºC (68-77ºF)

INACTIVE INGREDIENT SECTION

FD&C blue 1, FD&C red 3, FD&C red 40, ferroso ferric oxide, gelatin, hydroxypropyl cellulose, hypromellose, magnesium stearate, methacrylic acid and ethyl acrylate copolymer dispersion, mono and di-glycerides, polysorbate 80, potassium hydroxide, shellac, sodium lauryl sulfate, sugar spheres (contains corn starch, sucrose), talc, titanium dioxide, triethyl citrate

QUESTIONS OR COMMENTS?

Call 1-800-883-3540 (Monday - Friday 8 am - 4 pm)

OTHER SAFETY INFORMATION

Tips of Managing Heartburn

- Avoid foods or drinks that are more likely to cause heartburn, such as rich, spicy, fatty and fried foods, chocolate, caffeine, alcohol and even some acidic fruits and vegetables.
- Eat slowly and do not eat big meals.
- Do not eat late at night or just before bedtime.
- Do not lie flat or bend over soon after eating.
- Raise the head of your bed.
- Wear loose-fitting clothing around your stomach.
- If you are overweight, lose weight.
- If you smoke, quit smoking.

Do not use if seal under bottle cap imprinted with “SEALED FOR YOUR PROTECTION” or blue band around the center of each capsule is broken or missing.

KEEP CARTON FOR COMPLETE WARNINGS AND IMPORTANT INFORMATION.

PRINCIPAL DISPLAY PANEL

NDC 53041-666-07

See new warning information

Esomeprazole Magnesium

Delayed-Release Capsules USP, 20 mg*

Acid Reducer

Treats Frequent Heartburn

24 HR Capsules

May take 1 to 4 days for full effect

14 CAPSULES - One 14-day course of treatment